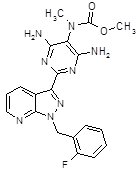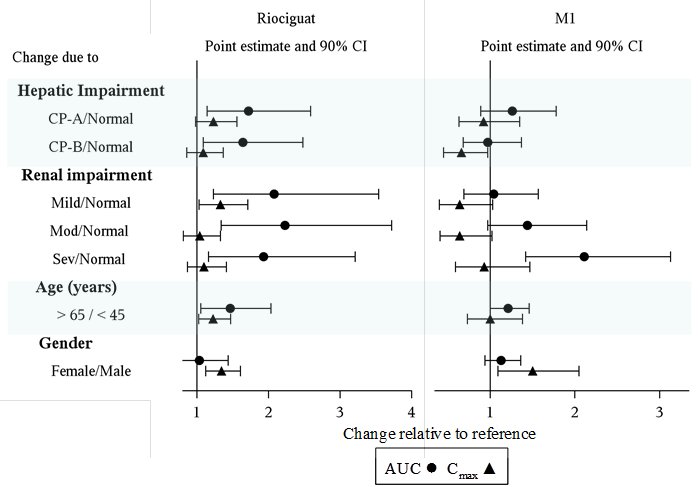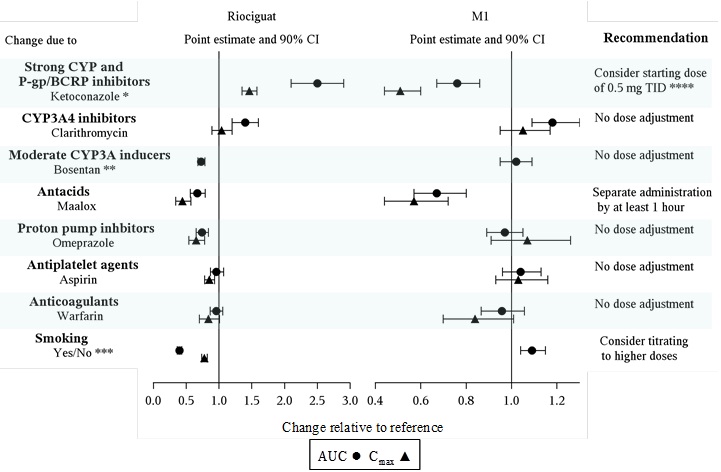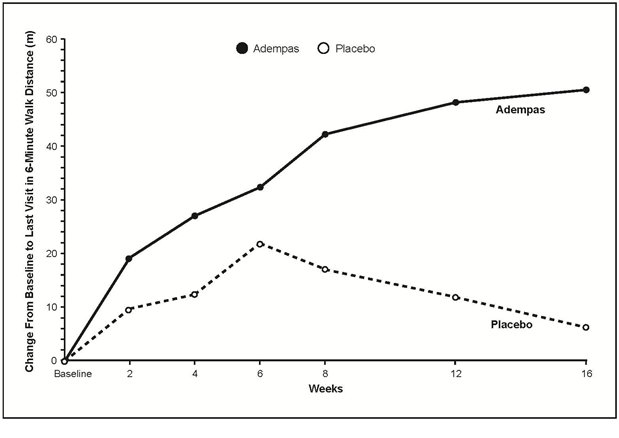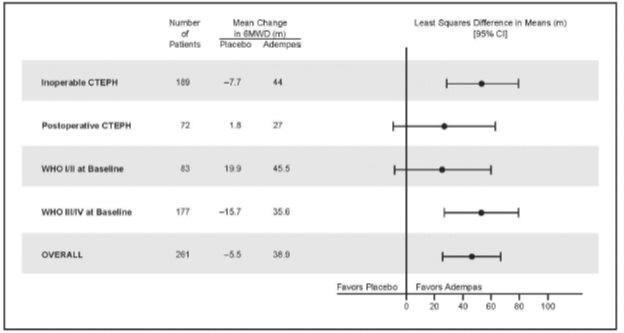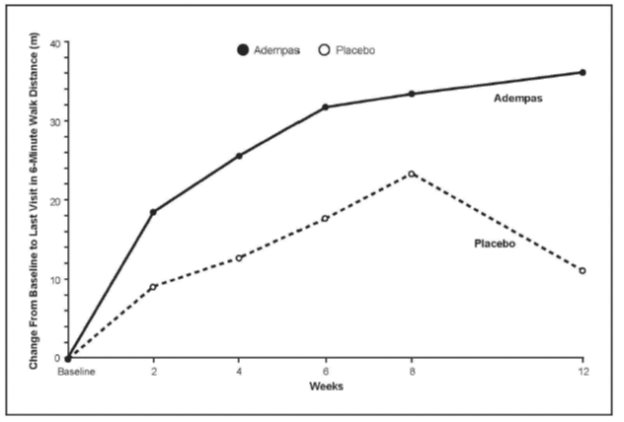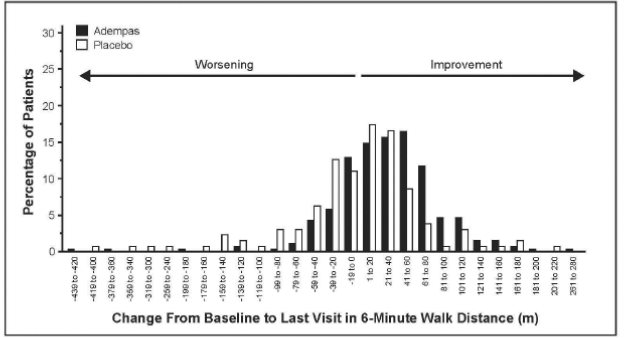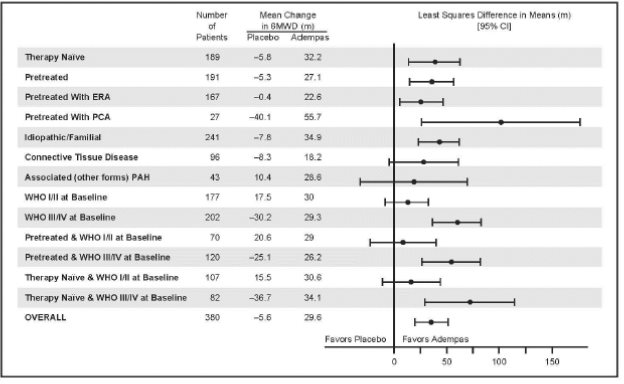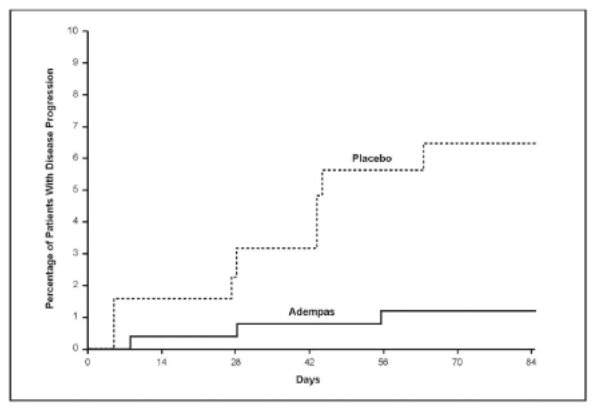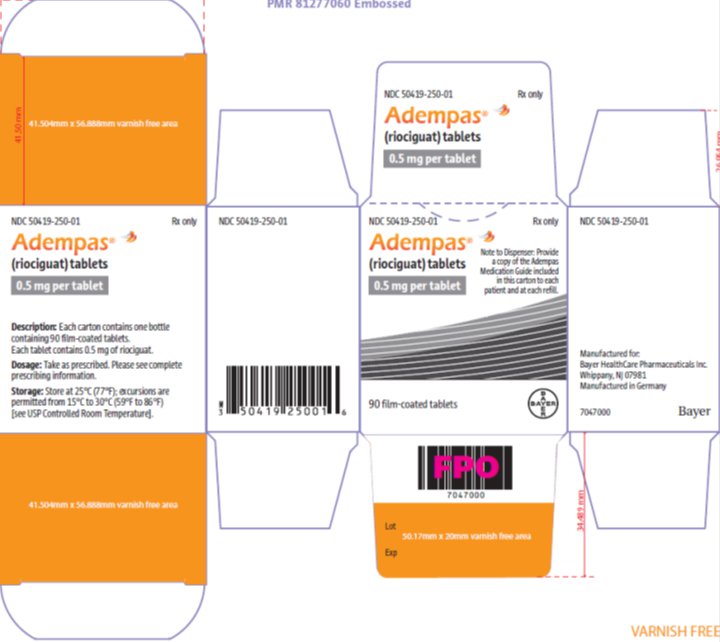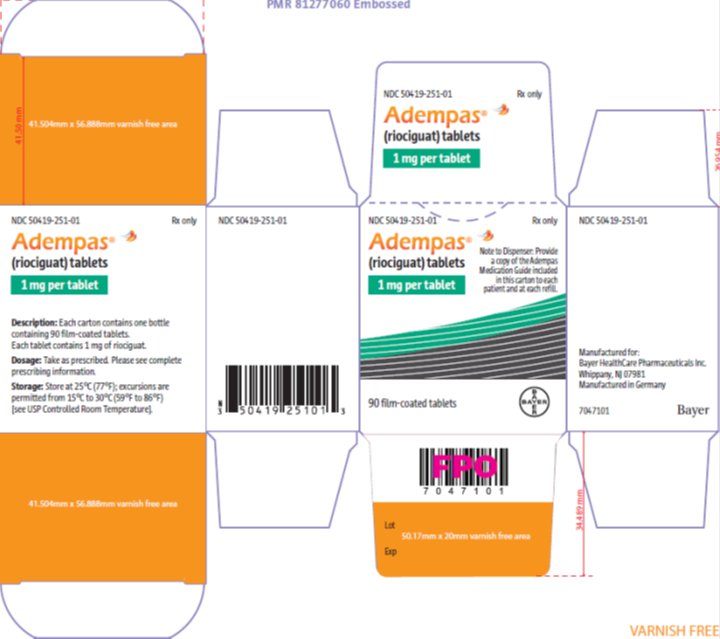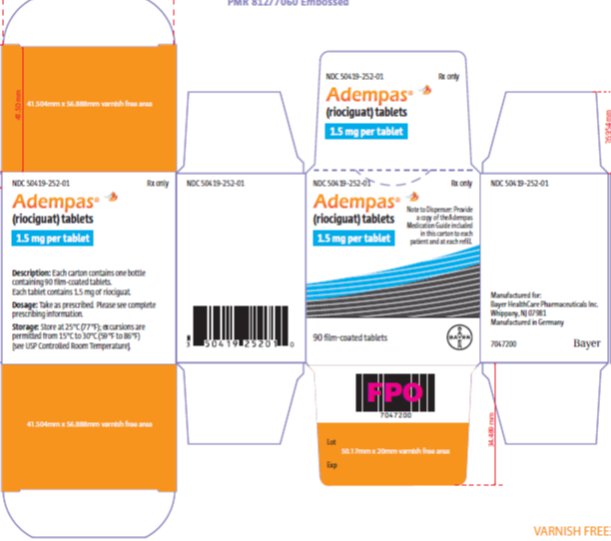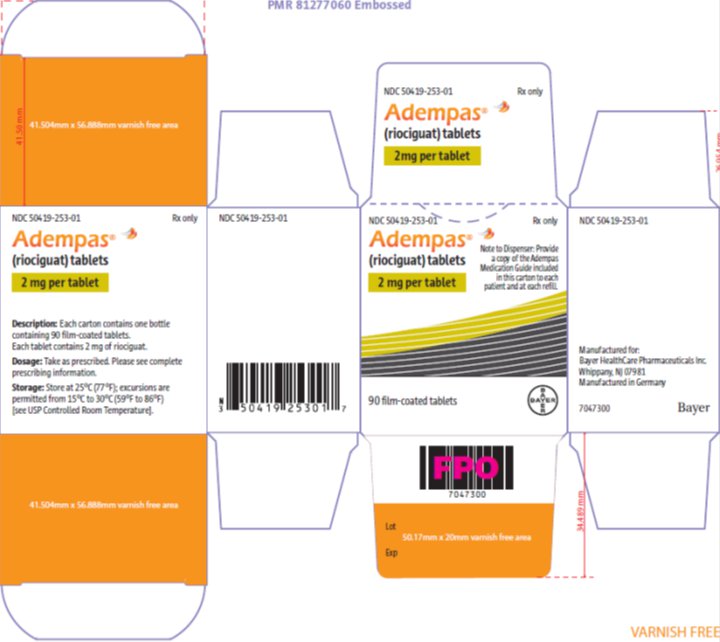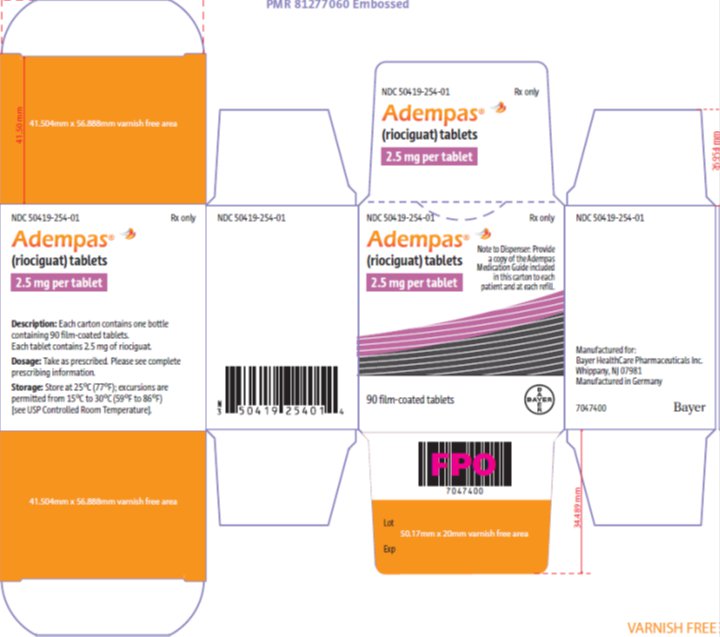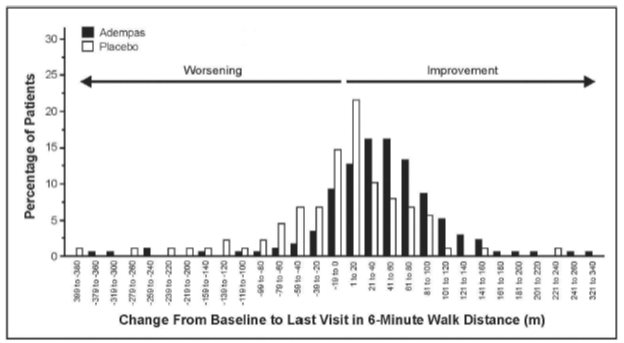 DRUG LABEL: Adempas
NDC: 50419-250 | Form: TABLET, FILM COATED
Manufacturer: Bayer HealthCare Pharmaceuticals Inc.
Category: prescription | Type: HUMAN PRESCRIPTION DRUG LABEL
Date: 20260302

ACTIVE INGREDIENTS: RIOCIGUAT 0.5 mg/1 1
INACTIVE INGREDIENTS: MICROCRYSTALLINE CELLULOSE; CROSPOVIDONE (120 .MU.M); HYPROMELLOSE, UNSPECIFIED; LACTOSE MONOHYDRATE; MAGNESIUM STEARATE; SODIUM LAURYL SULFATE; HYDROXYPROPYL CELLULOSE (1600000 WAMW); PROPYLENE GLYCOL; TITANIUM DIOXIDE

HIGHLIGHTS OF PRESCRIBING INFORMATION

These highlights do not include all the information needed to use ADEMPAS safely and effectively. See full prescribing information for ADEMPAS.
ADEMPAS (riociguat) tablets, for oral use
Initial U.S. Approval: 2013

WARNING: EMBRYO-FETAL TOXICITY

See full prescribing information for complete boxed warning.

- Based on animal data Adempas may cause fetal harm if used during pregnancy. (4.1, 5.1, 8.1)
- Females of reproductive potential: Confirm negative pregnancy status before the start of treatment. Use effective contraception prior to initiation of treatment, during treatment, and for one month after treatment with Adempas. (2.3, 5.1 8.6)
- When pregnancy is detected, discontinue Adempas as soon as possible (5.1)

RECENT MAJOR CHANGES

Boxed Warning | X/XXXX
Dosage and Administration (2.3) | X/XXXX
Warnings and Precautions (5.1) | X/XXXX
Warnings and Precautions (5.2)Adempas REMS Program(Removed) | X/XXXX

1 INDICATIONS AND USAGE

Adempas is a soluble guanylate cyclase (sGC) stimulator indicated for the treatment of adults with:

- Persistent/recurrent Chronic Thromboembolic Pulmonary Hypertension (CTEPH) (WHO Group 4) after surgical treatment or inoperable CTEPH to improve exercise capacity and WHO functional class. (1.1)
- Pulmonary Arterial Hypertension (PAH) (WHO Group 1) to improve exercise capacity, improve WHO functional class and to delay clinical worsening. (1.2)

2 DOSAGE AND ADMINISTRATION

- Initiate treatment at 1 mg taken three times a day. (2.1)
- For patients who may not tolerate the hypotensive effect of Adempas, consider a starting dose of 0.5 mg, three times a day. (2.1)
- Increase dosage by 0.5 mg at intervals of no sooner than 2-weeks as tolerated to a maximum of 2.5 mg three times a day. (2.1)
- Tablets may be crushed and mixed with water or soft foods for patients who have difficulty swallowing. (2.1)

3 DOSAGE FORMS AND STRENGTHS

Tablets: 0.5 mg, 1 mg, 1.5 mg, 2 mg and 2.5 mg (3)

4 CONTRAINDICATIONS

- Pregnancy (4.1)
- Use with nitrates or nitric oxide donors in any form (4.2, 7.1)
- Use with PDE inhibitors (2.6, 4.3, 7.1)
- Patients with concomitant use of other soluble guanylate cyclase (sGC) stimulators. (4.4, 7.1)
- Pulmonary hypertension associated with idiopathic interstitial pneumonias (PH-IIP) (4.5)

5 WARNINGS AND PRECAUTIONS

- Symptomatic hypotension (5.2)
- Bleeding (5.3)
- Pulmonary edema in patients with pulmonary veno-occlusive disease. If confirmed, discontinue treatment (5.4)

6 ADVERSE REACTIONS

Adverse reactions occurring more frequently (≥3%) on Adempas compared to placebo are headache, dyspepsia/gastritis, dizziness, nausea, diarrhea, hypotension, vomiting, anemia, gastroesophageal reflux, and constipation. (6.1)

To report SUSPECTED ADVERSE REACTIONS, contact Bayer HealthCare Pharmaceuticals Inc. at 1-888-842-2937 or FDA at 1-800-FDA-1088 or www.fda.gov/medwatch.

7 DRUG INTERACTIONS

- Strong CYP and P-gp/BCRP inhibitors: For patients receiving strong CYP and P-gp/BCRP inhibitors, consider a starting dose of 0.5 mg three times a day. Monitor for hypotension. (7.2)
- Antacids: Separate administration by at least 1 hour. (7.2)

8 USE IN SPECIFIC POPULATIONS

- Lactation: Advise not to breastfeed. (8.2)
- Renal impairment: Not recommended in patients with creatinine clearance <15 mL/min or on dialysis. (8.7)
- Hepatic impairment: Not recommended in patients with severe (Child Pugh C) hepatic impairment. (8.8)
- Smoking: May require dosages higher than 2.5 mg three times a day if tolerated. Dose decrease may be required in patients who stop smoking. (2.4, 7.2)

FULL PRESCRIBING INFORMATION

WARNING: EMBRYO-FETAL TOXICITY

Adempas is contraindicated for use during pregnancy because it may cause fetal harm based on animal data [see Contraindications (4.1), Warnings and Precautions (5.1), and Use in Specific Populations (8.1)].

Females of reproductive potential: Confirm negative pregnancy status before the start of treatment. Use effective contraception prior to initiation of treatment, during treatment, and for one month after treatment with Adempas [see Dosage and Administration (2.3), Warnings and Precautions (5.1),and Use in Specific Populations (8.3)].

When pregnancy is detected, discontinue Adempas as soon as possible [see Warnings and Precautions (5.1)].

1 INDICATIONS AND USAGE

1.1 Chronic-Thromboembolic Pulmonary Hypertension

Adempas is indicated for the treatment of adults with persistent/recurrent chronic thromboembolic pulmonary hypertension (CTEPH), (WHO Group 4) after surgical treatment, or inoperable CTEPH, to improve exercise capacity and WHO functional class [see Clinical Studies (14.1)].

1.2 Pulmonary Arterial Hypertension

Adempas is indicated for the treatment of adults with pulmonary arterial hypertension (PAH), (WHO Group 1), to improve exercise capacity, WHO functional class and to delay clinical worsening.

Efficacy was shown in patients on Adempas monotherapy or in combination with endothelin receptor antagonists or prostanoids. Studies establishing effectiveness included predominately patients with WHO functional class II–III and etiologies of idiopathic or heritable PAH (61%) or PAH associated with connective tissue diseases (25%) [see Clinical Studies (14.2)].

2 DOSAGE AND ADMINISTRATION

2.1 Recommended Dosage in Adult Patients

The recommended starting dosage is 1 mg taken 3 times a day. For patients who may not tolerate the hypotensive effect of Adempas, consider a starting dose of 0.5 mg taken three times a day. If systolic blood pressure remains greater than 95 mmHg and the patient has no signs or symptoms of hypotension, up-titrate the dose by 0.5 mg taken three times a day. Dose increases should be no sooner than 2 weeks apart. The dose can be increased to the highest tolerated dosage, up to a maximum of 2.5 mg taken three times a day. If at any time, the patient has symptoms of hypotension, decrease the dosage by 0.5 mg taken three times a day.

Crushed Tablets

For patients who are unable to swallow whole tablets, Adempas may be crushed and mixed with water or soft foods (such as applesauce) immediately before administration [see Clinical Pharmacology (12.3)].

2.2 Dosage Interruption

If a dose is missed, advise patients to continue with the next regularly scheduled dose.

In case Adempas is interrupted for 3 days or more, re-titrate Adempas.

2.3 Pregnancy Testing in Females of Reproductive Potential

Confirm negative pregnancy status prior to start of treatment. [see Use in Specific Populations (8.3)].

2.4 Use in Patients who Smoke

Consider titrating to dosages higher than 2.5 mg three times a day, if tolerated, in patients who smoke. A dose decrease may be required in patients who stop smoking [see Drug Interactions (7.2) and Clinical Pharmacology (12.3)].

2.5 Strong CYP and P-gp/BCRP Inhibitors

Consider a starting dose of 0.5 mg, three times a day when initiating Adempas in patients receiving strong cytochrome P450 (CYP) and P-glycoprotein/breast cancer resistance protein (P-gp/BCRP) inhibitors such as azole antimycotics (for example, ketoconazole, itraconazole) or HIV protease inhibitors (for example, ritonavir). Monitor for signs and symptoms of hypotension on initiation and on treatment with strong CYP and P-gp/BCRP inhibitors [see Warnings and Precautions (5.2), Drug Interactions (7.2) and Clinical Pharmacology (12.3)].

2.6 Transitioning to and from Adempas

- Discontinue sildenafil at least 24 hours prior to administering Adempas [see Contraindications (4.3) and Drug Interactions (7)].
- Discontinue tadalafil at least 48 hours prior to administering Adempas [see Contraindications (4.3) and Drug Interactions (7)]. Consider initiating Adempas at a starting dose of 0.5 mg in patients at risk of hypotension [see Dosage and Administration (2.1)]. Monitor for signs and symptoms of hypotension on initiation.
- Discontinue Adempas at least 24 hours prior to administering a PDE5-inhibitor [see Dosage and Administration (2.1), Contraindications (4.3), and Drug Interactions (7)]. Monitor for signs and symptoms of hypotension on initiation.

3 DOSAGE FORMS AND STRENGTHS

Tablets: film-coated, round, bi-convex:

- 0.5 mg, white, with "BAYER" cross on one side and "0.5" and "R" on the other side
- 1 mg, pale-yellow, with "BAYER" cross on one side and "1" and "R" on the other side
- 1.5 mg, yellow-orange, with "BAYER" cross on one side and "1.5" and "R" on the other side
- 2 mg, pale orange, with "BAYER" cross on one side and "2" and "R" on the other side
- 2.5 mg, red-orange, with "BAYER" cross on one side and "2.5" and "R" on the other side

4 CONTRAINDICATIONS

4.1 Pregnancy

Based on data from animal reproduction studies, Adempas may cause fetal harm when administered to a pregnant woman and is contraindicated in females who are pregnant. Adempas was consistently shown to have teratogenic effects when administered to animals. If this drug is used during pregnancy, or if the patient becomes pregnant while taking this drug, the patient should be apprised of the potential hazard to the fetus [see Use in Specific Populations (8.1)].

4.2 Nitrates and Nitric Oxide Donors

Co-administration of Adempas with nitrates or nitric oxide donors (such as amyl nitrite) in any form is contraindicated [see Drug Interactions (7.1) and Clinical Pharmacology (12.2)].

4.3 Phosphodiesterase Inhibitors

Concomitant administration of Adempas with specific PDE-5 inhibitors (such as sildenafil, tadalafil, or vardenafil) or nonspecific PDE-5 inhibitors (such as dipyridamole or theophylline) is contraindicated [see Dosage and Administration (2.6), Drug Interactions (7.1) and Clinical Pharmacology (12.2)]. Do not administer within 24 hours of sildenafil. Do not administer 24 hours before or within 48 hours after tadalafil.

4.4 Soluble Guanylate Cyclase Stimulators

Adempas is contraindicated in patients with concomitant use of other soluble guanylate cyclase (sGC) stimulators [see Drug Interactions (7.1)].

4.5 Pulmonary Hypertension Associated with Idiopathic Interstitial Pneumonias (PH-IIP)

Adempas is contraindicated in patients with pulmonary hypertension associated with idiopathic interstitial pneumonias (PH-IIP).

5 WARNINGS AND PRECAUTIONS

5.1 Embryo-Fetal Toxicity

Based on data from animal reproduction studies, Adempas may cause embryo-fetal toxicity when administered to a pregnant female and is contraindicated in females who are pregnant. The available human data for sGCs do not establish the presence or absence of major birth defects related to the use of Adempas. Advise females of reproductive potential of the potential risk to a fetus. Confirm negative pregnancy status before the start of treatment. Advise females of reproductive potential to use effective contraception prior to initiation of treatment, during treatment with ADEMPAS and for at least one month after the last dose. When pregnancy is detected, discontinue Adempas as soon as possible [see Dosage and Administration (2.3) and Use in Specific Populations (8.1, 8.3)].

5.2 Hypotension

Adempas reduces blood pressure. Consider the potential for symptomatic hypotension or ischemia in patients with hypovolemia, severe left ventricular outflow obstruction, resting hypotension, autonomic dysfunction, or concomitant treatment with antihypertensives or strong CYP and P-gp/BCRP inhibitors [see Drug Interactions (7.2) and Clinical Pharmacology (12.3)]. Consider a dose reduction if patient develops signs or symptoms of hypotension.

5.3 Bleeding

In the placebo-controlled clinical trials, serious bleeding occurred in 2.4% of patients taking Adempas compared to 0% of placebo patients. Serious hemoptysis occurred in 5 (1%) patients taking Adempas compared to 0 placebo patients, including one event with fatal outcome. Serious hemorrhagic events also included 2 patients with vaginal hemorrhage, 2 with catheter site hemorrhage, and 1 each with subdural hematoma, hematemesis, and intra-abdominal hemorrhage.

5.4 Pulmonary Veno-Occlusive Disease

Pulmonary vasodilators may significantly worsen the cardiovascular status of patients with pulmonary veno-occlusive disease (PVOD). Therefore, administration of Adempas to such patients is not recommended. Should signs of pulmonary edema occur, the possibility of associated PVOD should be considered and, if confirmed, discontinue treatment with Adempas.

6 ADVERSE REACTIONS

The following serious adverse reactions are discussed elsewhere in the labeling:

- Embryo-Fetal Toxicity [see Warnings and Precautions (5.1)]
- Hypotension [see Warnings and Precautions (5.2)]
- Bleeding [see Warnings and Precautions (5.3)]

6.1 Clinical Trials Experience

Because clinical trials are conducted under widely varying conditions, adverse reaction rates observed in the clinical trials of a drug cannot be directly compared to rates in the clinical trials of another drug and may not reflect the rates observed in practice.

The safety data described below reflect exposure to Adempas in two, randomized, double blind, placebo-controlled trials in patients with inoperable or recurrent/persistent CTEPH (CHEST-1) and treatment naive or pre-treated PAH patients (PATENT-1). The population (Adempas: n = 490; Placebo: n = 214) was between the age of 18 and 80 years [see Clinical Studies (14.1, 14.2)].

The safety profile of Adempas in patients with inoperable or recurrent/persistent CTEPH (CHEST-1) and treatment naive or pre-treated PAH (PATENT-1) were similar. Therefore, adverse drug reactions (ADRs) identified from the 12 and 16 week placebo-controlled trials for PAH and CTEPH respectively were pooled, and those occurring more frequently on Adempas than placebo (≥3%) are displayed in Table 1 below. Most adverse reactions in Table 1 can be ascribed to the vasodilatory mechanism of action of Adempas.

The overall rates of discontinuation due to an adverse event in the pivotal placebo-controlled trials were 2.9% for Adempas and 5.1% for placebo (pooled data).

Table 1: Adverse Reactions Occurring More Frequently (≥3%) on Adempas than Placebo (Pooled from CHEST-1 and PATENT-1)
Adverse Reactions | Adempas %; (n=490) | Placebo %; (n=214)
Headache | 27 | 18
Dyspepsia and Gastritis | 21 | 8
Dizziness | 20 | 13
Nausea | 14 | 11
Diarrhea | 12 | 8
Hypotension | 10 | 4
Vomiting | 10 | 7
Anemia (including laboratory parameters) | 7 | 2
Gastroesophageal reflux disease | 5 | 2
Constipation | 5 | 1

Other events that were seen more frequently in Adempas compared to placebo and potentially related to treatment were: palpitations, nasal congestion, epistaxis, dysphagia, abdominal distension and peripheral edema. With longer observation in uncontrolled long-term extension studies the safety profile was similar to that observed in the placebo controlled phase 3 trials.

7 DRUG INTERACTIONS

7.1 Pharmacodynamic Interactions with Adempas

Other Soluble Guanylate Cyclase Stimulators: Co-administration of Adempas is contraindicated in patients with use of other soluble guanylate cyclase (sGC) stimulators [see Contraindications (4.4)].

Nitrates: Co-administration of Adempas with nitrates or nitric oxide donors (such as amyl nitrite) in any form is contraindicated because of hypotension [see Contraindications (4.2) and Clinical Pharmacology (12.2)].

PDE Inhibitors: Co-administration of Adempas with specific PDE-5 inhibitors (such as sildenafil, tadalafil, or vardenafil) and nonspecific PDE inhibitors (such as dipyridamole or theophylline), is contraindicated because of hypotension. Do not administer within 24 hours of sildenafil. Do not administer 24 hours before or within 48 hours after tadalafil [see Dosage and Administration (2.6)]. Clinical experience with co-administration of Adempas and other phosphodiesterase inhibitors (for example, milrinone, cilostazole, roflumilast) is limited.

7.2 Pharmacokinetic Interactions with Adempas

Smoking: Plasma concentrations in smokers are reduced by 50% to 60% compared to nonsmokers. Based on pharmacokinetic modeling, for patients who are smokers, doses higher than 2.5 mg three times a day may be considered in order to match exposure seen in nonsmoking patients. Safety and effectiveness of Adempas doses higher than 2.5 mg three times a day have not been established. A dose reduction should be considered in patients who stop smoking [see Dosage and Administration (2.4) and Clinical Pharmacology (12.3)].

Strong CYP and P-gp/BCRP inhibitors: Concomitant use of riociguat with strong cytochrome CYP inhibitors and P-gp/BCRP inhibitors such as azole antimycotics (for example, ketoconazole, itraconazole) or HIV protease inhibitors (such as ritonavir) increase riociguat exposure and may result in hypotension. Consider a starting dose of 0.5 mg 3 times a day when initiating Adempas in patients receiving strong CYP and P-gp/BCRP inhibitors. Monitor for signs and symptoms of hypotension on initiation and on treatment with strong CYP and P-gp/BCRP inhibitors. A dose reduction should be considered in patients who may not tolerate the hypotensive effect of riociguat [see Dosage and Administration (2.5), Warnings and Precautions (5.2) and Clinical Pharmacology (12.3)].

Strong CYP3A inducers: Strong inducers of CYP3A (for example, rifampin, phenytoin, carbamazepine, phenobarbital or St. John's Wort) may significantly reduce riociguat exposure. Data are not available to guide dosing of riociguat when strong CYP3A inducers are co-administered [see Clinical Pharmacology (12.3)].

Antacids: Antacids such as aluminum hydroxide/magnesium hydroxide decrease riociguat absorption and should not be taken within 1 hour of taking Adempas [see Clinical Pharmacology (12.3)].

8 USE IN SPECIFIC POPULATIONS

8.1 Pregnancy

Risk Summary

Based on data from animal reproduction studies, Adempas may cause embryo-fetal toxicity and miscarriage when administered to a pregnant woman and is contraindicated during pregnancy [see Contraindications (4.1)]. Available data from postmarketing reports have not identified an increased risk of major birth defects; however, these data are limited. Methodological limitations of these postmarketing reports include lack of a control group; limited information regarding dose, duration, and timing of drug exposure; and missing data. These limitations preclude establishing a reliable estimate of the risk of adverse fetal and neonatal outcomes with maternal sGC use. In animal reproduction studies, oral administration of riociguat to pregnant rats during organogenesis was teratogenic and embryotoxic at exposures approximately 8 times and 2 times, respectively, the human exposure. In reproduction studies with pregnant rabbits, oral administration of riociguat during organogenesis caused abortions and fetal toxicity at exposures approximately 4 times and 13 times, respectively, the maximum recommended human dose (MRHD). Advise pregnant women of the potential risk to a fetus.

The estimated background risk of major birth defects and miscarriage for the indicated population is unknown. All pregnancies have a background risk of birth defect, loss, or other adverse outcomes. In the U.S. general population, the estimated background risk of major birth defects and miscarriage in clinically recognized pregnancies is 2–4% and 15–20%, respectively.

Data

Animal Data

In rats administered riociguat orally (1, 5, and 25 mg/kg/day) throughout organogenesis, an increased rate of cardiac ventricular-septal defect was observed at the highest dose tested. The highest dose produced evidence of maternal toxicity (reduced body weight). Post-implantation loss was statistically significantly increased from the mid-dose of 5 mg/kg/day. Plasma exposure at the lowest dose in which no adverse effects were observed is approximately 0.4 times that in humans at the maximally recommended human dose (MRHD) of 2.5 mg three times a day based on area under the time-concentration curve (AUC) for unbound drug in rat and humans. Plasma exposure at the highest dose (25 mg/kg/day) is approximately 8 times that in humans at the MRHD while exposure at the mid-dose (5 mg/kg/day) is approximately 2 times that in humans at the MRHD. In rabbits given doses of 0.5, 1.5 and 5 mg/kg/day, an increase in spontaneous abortions was observed starting at the middle dose of 1.5 mg/kg, and an increase in resorptions was observed at 5 mg/kg/day. Plasma exposures at these doses were 4 times and 13 times, respectively, the human exposure at the MRHD.

8.2 Lactation

Risk Summary

There are no data on the presence of riociguat in human milk, the effects on the breastfed infant, or the effect on milk production. Riociguat is present in rat milk. Because of the potential for serious adverse reactions from ADEMPAS, such as hypotension, in breastfed infants, advise women not to breastfeed during treatment with ADEMPAS.

8.3 Females and Males of Reproductive Potential

Pregnancy Testing

Confirm female patients of reproductive potential have a negative pregnancy status prior to starting treatment with Adempas. Advise patients to contact their healthcare provider if they become pregnant or suspect they may be pregnant. Counsel patients on the risk to the fetus [see Boxed Warning, Dosage and Administration (2.3) and Use in Specific Populations (8.1)].

Contraception

Females

Female patients of reproductive potential must use effective contraception prior to initiation of treatment, during treatment with Adempas and for 1 month after treatment with Adempas to prevent pregnancy. [see Boxed Warning].

8.4 Pediatric Use

Safety and effectiveness of Adempas in pediatric patients have not been established [see Nonclinical Toxicology (13.2)].

8.5 Geriatric Use

Of the total number of subjects in clinical studies of Adempas, 23% were 65 and over, and 6% were 75 and over [see Clinical Studies (14)]. No overall differences in safety or effectiveness were observed between these subjects and younger subjects, and other reported clinical experience has not identified differences in responses between the elderly and younger patients, but greater sensitivity of some older individuals cannot be ruled out.

Elderly patients showed a higher exposure to Adempas [see Clinical Pharmacology (12.3)].

8.6 Renal Impairment

Safety and efficacy have not been demonstrated in patients with creatinine clearance <15 mL/min or on dialysis [see Clinical Pharmacology (12.3)].

8.7 Hepatic Impairment

Safety and efficacy have not been demonstrated in patients with severe hepatic impairment (Child Pugh C) [see Clinical Pharmacology (12.3)].

10 OVERDOSAGE

In cases of overdose, blood pressure should be closely monitored and supported as appropriate. Based on extensive plasma protein binding, riociguat is not expected to be dialyzable.

11 DESCRIPTION

Adempas (riociguat) is a soluble guanylate cyclase stimulator tablet for oral administration. Riociguat is methyl 4,6-diamino-2-[1-(2-fluorobenzyl)-1H-pyrazolo [3,4-b]pyridin-3-yl]-5-pyrimidinyl(methyl)carbamate with the following structural formula:

C20H19FN8O2

Riociguat is a white to yellowish, crystalline, non-hygroscopic substance with a molecular weight of 422.42 g/mol. In solid form it is stable to temperature, light, and humidity.

The solubility at 25°C in water: 4 mg/L, in ethanol: 800 mg/L, in 0.1 HCl (pH 1): 250 mg/L and in buffer (phosphate) pH 7: 3 mg/L. In the pH range of 2 to 4 the solubility showed strong pH-dependency. Solubility increases at lower pH values.

Each round film-coated tablet contains 0.5 mg (1.0, 1.5, 2.0, 2.5 mg) riociguat. The inactive ingredients are cellulose microcrystalline, crospovidone, hypromellose 5cP, lactose monohydrate, magnesium stearate, sodium laurylsulfate, hydroxypropylcellulose, hypromellose 3cP, propylene glycol, and titanium dioxide. Adempas 1, 1.5, 2, and 2.5 mg tablets contain, in addition, ferric oxide yellow. Adempas 2 and 2.5 mg tablets contain, in addition, ferric oxide red.

12 CLINICAL PHARMACOLOGY

12.1 Mechanism of Action

Riociguat is a stimulator of soluble guanylate cyclase (sGC), an enzyme in the cardiopulmonary system and the receptor for nitric oxide (NO).

When NO binds to sGC, the enzyme catalyzes synthesis of the signaling molecule cyclic guanosine monophosphate (cGMP). Intracellular cGMP plays an important role in regulating processes that influence vascular tone, proliferation, fibrosis and inflammation.

Pulmonary hypertension is associated with endothelial dysfunction, impaired synthesis of nitric oxide and insufficient stimulation of the NO-sGC-cGMP pathway.

Riociguat has a dual mode of action. It sensitizes sGC to endogenous NO by stabilizing the NO-sGC binding. Riociguat also directly stimulates sGC via a different binding site, independently of NO.

Riociguat stimulates the NO-sGC-cGMP pathway and leads to increased generation of cGMP with subsequent vasodilation.

The active metabolite (M1) of riociguat is 1/3 to 1/10 as potent as riociguat.

12.2 Pharmacodynamics

There is a direct relationship between riociguat plasma concentration and hemodynamic parameters such as systemic vascular resistance, systolic blood pressure, pulmonary vascular resistance (PVR), and cardiac output [see Clinical Studies (14)].

Hemodynamic parameters were assessed in CTEPH patients in CHEST-1 [see Clinical Studies (14.1)]. Right heart catheterization was performed at the beginning and the end of the study period in 233 patients. A statistically significant reduction of PVR (-246 dyn*s*cm^-5) was shown in the Adempas group vs. placebo. Improvements in other hemodynamic parameters (not pre-specified as endpoints) are displayed in Table 2 below.

Table 2: CHEST-1, Change In Hemodynamic Parameters from Baseline to Last Visit (Individual Dose Titration to Maximum 2.5 mg Three Times a Day versus placebo)
Parameter (unit) | Mean change |  | LS mean difference | 95% CI
 | Adempas | Placebo
Pulmonary Capillary Wedge Pressure (mmHg) | 0.59 | 0.18 | 0.58 | –0.36 to 1.53
Right Atrial Pressure (mmHg) | –1.04 | –0.55 | –0.55 | –1.72 to 0.62
Pulmonary Arterial Pressure Systolic (mmHg) | –6.84 | 0.95 | –7.52 | –10.88 to –4.16
Pulmonary Arterial Pressure Diastolic (mmHg) | –3.05 | 0.67 | –3.62 | –5.30 to –1.95
Pulmonary Arterial Pressure Mean (mmHg) | –4.31 | 0.76 | –4.96 | –6.75 to –3.16
Mean Arterial Pressure (mmHg) | –9.27 | –0.29 | –9.15 | –11.83 to –6.46
Mixed Venous Oxygen Saturation (%) | 2.95 | –0.44 | 3.85 | 1.46 to 6.25
Cardiac Output (L/min) | 0.81 | –0.03 | 0.86 | 0.59 to 1.12
Cardiac Index (L/min/m^2) | 0.45 | –0.01 | 0.47 | 0.33 to 0.62
Pulmonary Vascular Resistance (dyn*s*cm^-5) | –226 | 23.1 | –246 | –303 to –190
Pulmonary Vascular Resistance Index (dyn*s*cm^-5*m^2) | –397 | 48.3 | –449 | –554 to –344
Systemic Vascular Resistance (dyn*s*cm^-5) | –445 | 16.6 | –478 | –602 to –354
Systemic Vascular Resistance Index (dyn*s*cm^-5*m^2) | –799 | 53.7 | –914 | –1141 to –687

Hemodynamic parameters were assessed in PAH patients in PATENT-1 [see Clinical Studies (14.2)]. Right heart catheterization was performed at the beginning and the end of the study period in 339 patients.

A statistically significant reduction of PVR (-226 dyn*sec*cm^-5) was shown in the Adempas individual titration group (to maximum dose of 2.5 mg three times a day) vs. placebo. Improvement in other relevant hemodynamic parameters (not pre-specified as endpoints) for the individual dose titration group versus placebo are displayed in Table 3.

Table 3: PATENT-1, Change in Hemodynamic Parameters from Baseline to Last Visit (Individual Dose Titration to Maximum 2.5 mg Three Times a Day versus Placebo)
Parameter (unit) | Mean change |  | LS mean difference | 95% CI
 | Adempas | Placebo
Pulmonary Capillary Wedge Pressure (mmHg) | 1.08 | 0.46 | 0.41 | –0.36 to 1.18
Right Atrial Pressure (mmHg) | –0.20 | 0.97 | –1.01 | –2.15 to 0.13
Pulmonary Arterial Pressure Systolic (mmHg) | –5.39 | 0.78 | –6.73 | –9.43 to –4.04
Pulmonary Arterial Pressure Diastolic (mmHg) | –3.19 | –1.12 | –2.41 | –4.15 to –0.68
Pulmonary Arterial Pressure mean (mmHg) | –3.93 | –0.5 | –3.83 | –5.61 to –2.06
Mean Arterial Pressure (mmHg) | –8.54 | –1.4 | –7.25 | –9.6 to –4.90
Mixed Venous Oxygen Saturation (%) | 3.15 | –2.33 | 5.02 | 3.2 to 6.84
Cardiac Output (L/min) | 0.93 | –0.01 | 0.93 | 0.7 to 1.15
Cardiac Index (L/min/m^2) | 0.54 | –0.02 | 0.56 | 0.44 to 0.69
Pulmonary Vascular Resistance (dyn*s*cm^-5) | –223 | –8.9 | –226 | –281 to –170
Pulmonary Vascular Resistance Index (dyn*s*cm^-5*m^2) | –374 | –22.4 | –377 | –469 to –285
Systemic Vascular Resistance (dyn*s*cm^-5) | –448 | –67.5 | –395 | –473 to –316
Systemic Vascular Resistance Index (dyn*s*cm^-5*m^2) | –753 | –130 | –675 | –801 to –550

Biomarkers

In the CHEST-1 study, Adempas significantly reduced N-terminal prohormone of brain natriuretic peptide (NT-proBNP), placebo-corrected mean change from baseline -444 ng/L, 95% CI -843 to -45. In the PATENT-1 study Adempas demonstrated a statistically significant reduction of NT-proBNP, placebo‑corrected mean change from baseline: -432 ng/L, 95% CI –782 to –82.

Pharmacodynamic interactions

Nitrates: Riociguat 2.5 mg tablets potentiated the blood pressure lowering effect of sublingual nitroglycerin (0.4 mg) taken 4 and 8 hours after riociguat. Syncope was reported in some patients [see Contraindications (4.2)].

Phosphodiesterase-5 inhibitors: In an exploratory interaction study in 7 patients with PAH on stable sildenafil treatment (20 mg three times a day), single doses of riociguat (0.5 mg and 1 mg sequentially) showed additive hemodynamic effects.

Among patients with PAH on stable sildenafil treatment (20 mg, three times a day) and riociguat (1 to 2.5 mg, three times a day) there was one death, possibly related to the combination of these drugs, and a high rate of discontinuation for hypotension [see Contraindications (4.3)].

Warfarin: Concomitant administration of riociguat and warfarin did not alter prothrombin time.

Acetylsalicylic Acid: Concomitant use of riociguat and aspirin did not affect bleeding time or platelet aggregation.

12.3 Pharmacokinetics

Riociguat pharmacokinetics are dose proportional from 0.5 to 2.5 mg. Inter-individual variability of riociguat exposure (AUC) across all doses is approximately 60%, and within-subject variability is approximately 30%.

Absorption and distribution

The absolute bioavailability of riociguat is about 94%. Peak plasma riociguat concentrations were observed within 1.5 hours after tablet intake. Food does not affect the bioavailability of riociguat.

Bioavailability (AUC and Cmax) of riociguat administered orally as a crushed tablet suspended in applesauce or in water is similar to that of a whole tablet.

The volume of distribution at steady state is approximately 30 L. Plasma protein binding in humans is approximately 95%, with serum albumin and α1–acidic glycoprotein being the main binding components.

Riociguat is a substrate of P-gp and BCRP.

Metabolism and excretion

Riociguat is mainly cleared through metabolism by CYP1A1, CYP3A4, CYP3A5 and CYP2J2. Formation of the major active metabolite, M1, is catalyzed by CYP1A1, which is inducible by polycyclic aromatic hydrocarbons such as those present in cigarette smoke. M1 is further metabolized to the inactive N-glucuronide. Plasma concentrations of M1 in patients with PAH are about half those for riociguat.

Following oral administration of radiolabeled riociguat in healthy individuals, about 40 and 53% of the total radioactivity was recovered in urine and feces, respectively. There appears to be considerable variability in the proportion of metabolites and unchanged riociguat excreted, but metabolites were the major components of the dose excreted in most individuals.

Average systemic clearance of riociguat was about 1.8 L/h in patients with PAH and about 3.4 L/h in healthy subjects. The terminal elimination half-life is about 12 hours in patients and 7 hours in healthy subjects.

Specific Populations: The effect of intrinsic factors on riociguat and M1 are shown below in Figure 1. There are no clinically relevant effects of age, sex, weight, or race/ethnicity on the pharmacokinetics of riociguat or M1. No dose adjustment is warranted.

Figure 1: Effect of Intrinsic Factors on Riociguat and M1 Pharmacokinetics

Drug interactions: The effect of extrinsic factors on riociguat and M1 were studied in healthy subjects and are shown in Figure 2.

Figure 2: Effect of Extrinsic Factors on Riociguat and M1 Pharmacokinetics

*HIV protease inhibitors are strong CYP3A inhibitors and may increase riociguat plasma concentrations to levels similar to those seen with ketoconazole. ** AUC only, estimated using population pharmacokinetics methods *** AUC only for metabolite, estimated using population pharmacokinetics methods. **** Monitor for signs and symptoms of hypotension on initiation and on treatment with strong CYP and P-gp/BCRP inhibitors [see Dosage and Administration (2.4, 2.5), Warnings and Precautions (5.2) and Drug Interactions (7.2)].

Strong CYP3A inducers: Data are not available to inform dosing of riociguat when strong CYP3A inducers are co-administered [see Drug Interactions (7.2)].

Effects of Riociguat on other Drugs: Riociguat did not affect the pharmacokinetics of midazolam, warfarin, or sildenafil [see Contraindications (4.3) and Clinical Pharmacology (12.2)].

Riociguat (2.5 mg three times per day) did not affect the systemic exposure of combined oral contraceptives containing levonorgestrel and ethinyl estradiol when concomitantly administered to healthy female subjects.

13 NONCLINICAL TOXICOLOGY

13.1 Carcinogenesis, Mutagenesis, Impairment of Fertility

Carcinogenesis: Carcinogenicity studies of riociguat were conducted in mice and rats. In mice, oral administration of riociguat (up to 25 mg/kg/day in males and 32 mg/kg/day in females) for up to two years did not demonstrate evidence of carcinogenesis. Plasma exposure (AUC) of unbound riociguat at the highest dose was 6 times the human's exposure.

In rats, oral administration of riociguat (up to 20 mg/kg/day) for up to two years did not demonstrate evidence of carcinogenesis. Plasma exposure (AUC) of unbound riociguat at the highest dose was 7 times the human exposure.

Mutagenesis: Riociguat and M1 did not show genotoxic potential in the in vitro bacterial reverse mutation (Ames) assay, the in vitro chromosomal aberration assay in Chinese hamster V79 cells, or the in vivo micronucleus assay in the mouse.

Impairment of fertility: In rats, no effects on male or female fertility were observed.

In male rats, oral administration of riociguat (up to 30 mg/kg/day) prior to and throughout the mating period had no effect on fertility. The no-effect dose for adverse effects is 37 times the human exposure when based on body surface area.

In female rats, oral administration of riociguat (up to 30 mg/kg/day) prior to and during mating and continuing to gestation Day 7 had no effect on fertility. The no-effect dose for adverse effects is 37 times the human exposure when based on body surface area.

13.2 Animal Toxicology

In growing rats, effects on bone formation were observed, including thickening of the growth plates, disorganized trabecular bone, and diffuse hyperostosis [see Use in Specific Populations (8.4)].

14 CLINICAL STUDIES

14.1 Chronic-Thromboembolic Pulmonary Hypertension

A double-blind, multi-national, multi-center, study (CHEST-1) was conducted in 261 patients with CTEPH. Patients were included if they:

- were technically inoperable for pulmonary endarterectomy, with PVR >300 dyn*sec*cm^-5 and mean pulmonary artery pressure >25 mmHg measured at least 90 days after the start of full anticoagulation, or
- had recurrent or persisting pulmonary hypertension defined as PVR > 300 dyn*sec*cm^-5 measured at least 180 days following pulmonary endarterectomy.

Patients were randomized to Adempas titrated up to 2.5 mg three times a day (n=173) or placebo (n=88). All patients were initiated at 1 mg three times a day. Patients with systolic blood pressure < 95 mmHg were excluded from the study. The dose of riociguat was titrated every 2 weeks based on the patient's systolic blood pressure and signs or symptoms of hypotension. Stable dosages of oral anticoagulants, diuretics, digitalis, calcium channel blockers and oxygen were allowed, but not concomitant therapy with NO donors, endothelin receptor antagonists, prostacyclin analogues (PCA), specific PDE-5 inhibitors (such as, sildenafil, tadalafil, or vardenafil), and nonspecific phosphodiesterase inhibitors (for example, dipyridamole or theophylline).

The primary endpoint of the study was change from baseline in six minute walking distance (6MWD) after 16 weeks. The mean age of the patients enrolled was 59 years (range 18–80 years). In the study, 72% of patients had inoperable CTEPH, 28% had recurrent or persisting pulmonary hypertension following pulmonary endarterectomy. The majority of patients had a World Health Organization (WHO) Functional Class II (31%) or III (64%) at baseline. The mean baseline 6MWD was 347 meters. In the study, 77% of patients were titrated to the maximum dose of 2.5 mg three times a day; 13%, 6%, 4%, and 1% of patients were titrated to riociguat doses of 2, 1.5, 1, and 0.5 mg three times a day, respectively.

Results of the 6MWD over 16 weeks for the CHEST-1 study are shown in Figure 3.

Figure 3: CHEST-1 Mean Change from Baseline in the 6-Minute Walk Distance

The pre-specified primary endpoint of the study was the change in 6MWD from baseline to week 16 and was based on imputed values. The imputation for missing values included last observed value, not including follow-up for patients who completed the study or withdrew. For deaths or clinical worsening without a termination visit or a measurement at that visit, the imputed worst value (zero) was used.

Improvements in walking distance were apparent from Week 2 onward. At Week 16, the placebo adjusted mean increase in 6MWD within the Adempas group was 46 m (95% confidence interval [CI]: 25 m to 67 m; p<0.0001). For CHEST-1, the median difference (Hodges-Lehmann non-parametric estimate) in 6MWD was 39 m (95% CI, 25 m to 54 m).

Figure 4 illustrates the results of the Adempas and placebo treatment groups displayed as a histogram summarizing the treatment effect on the 6MWD. The patients are grouped by change in 20 meters from baseline. Overall this figure shows that patients treated with Adempas benefit compared to those treated with placebo. As demonstrated in Figure 4, 143 patients receiving Adempas (83%) experienced an improvement in 6MWD compared to 50 patients (57%) on placebo.

Figure 4: CHEST-1 Distribution of Patients by Change from Baseline in 6-Minute Walk Distance

Placebo-adjusted changes in 6MWD at 16 weeks were evaluated in subgroups (see Figure 5).

Figure 5: Mean Treatment Difference in Change from Baseline to Last Visit in 6-Minute Walk Distance (meters) by Prespecified Subgroups

WHO Functional Class improvements in the CHEST-1 trial are shown in Table 4.

Table 4: Effects of Adempas on the Change in WHO Functional Class in CHEST-1 from Baseline to Week 16
Change in WHO Functional Class | Adempas (n=173) | Placebo (n=87)
Improved | 57 (33%) | 13 (15%)
Stable | 107 (62%) | 68 (78%)
Deteriorated | 9 (5%) | 6 (7%)
 | p-value=0.0026

Long Term Treatment of CTEPH

An open-label extension study (CHEST-2) included 237 patients who had completed CHEST-1. At the cut-off date in the CHEST-2 study, the mean treatment duration for the total population was 1077 days (± 433). The probabilities of survival at 1 and 2 years were 97% and 93%, respectively. Without a control group, however, these data must be interpreted cautiously.

14.2 Pulmonary Arterial Hypertension

A double-blind, multi-national, multi-center study (PATENT-1) was conducted in 443 patients with PAH as defined by PVR >300 dyn*sec*cm^-5 and a PAP mean >25 mmHg.

Patients were randomized to one of three treatment groups: Adempas titrated up to 1.5 mg (n=63), 2.5 mg (n=254) or placebo (n=126) three times a day. Patients with systolic blood pressure < 95 mmHg were excluded from the study. Patients assigned to Adempas were initiated at 1.0 mg three times a day. The dose of Adempas was up-titrated every 2 weeks based on the patient's systolic blood pressure and signs or symptoms of hypotension. Oral anticoagulants, diuretics, digitalis, calcium channel blockers, and oxygen were allowed. In this study, 50% of the patients were treatment-naive with respect to PAH therapy, 44% were pre-treated with an endothelin receptor antagonist (ERA) and 6% were pre-treated with a PCA (inhaled, oral or subcutaneous). Pre-treated patients were defined as patients on stable treatment for 3 months with either an ERA or PCA; Adempas was added in combination to these background therapies.

The primary endpoint of the study was change from baseline and placebo in 6MWD after 12 weeks in the 2.5 mg group. The mean age of all patients was 51 years and approximately 80% were female. PAH etiologies were either idiopathic (61%) or familial PAH (2%), PAH associated with connective tissue disease (25%), congenital heart disease (8%), portal hypertension (3%), or anorexigen or amphetamine use (1%). The majority of patients had a WHO Functional Class II (42%) or III (54%) at baseline. The overall mean baseline 6MWD was 363 meters. Approximately 75% of patients were up-titrated to receive the maximum dose of 2.5 mg three times a day by week 12; 15%, 6%, 3%, and 2% were titrated to doses of 2, 1.5, 1, and 0.5 mg 3 times a day, respectively.

Results of the 6MWD over 12 weeks for the PATENT-1 study are shown in Figure 6.

Figure 6: PATENT-1 Mean Change from Baseline in the 6-Minute Walk Distance

The pre-specified primary endpoint of the study was the change in 6MWD from baseline to week 12 and was based on imputed values. The imputation for missing values included last observed value, not including follow-up for patients who completed the study or withdrew. In case of death or clinical worsening without a termination visit or a measurement at that termination visit, the imputed worst value (zero) was used.

Figure 7 illustrates the results of the Adempas and placebo treatment groups displayed as a histogram summarizing the treatment effect on the 6MWD. The patients are grouped by change in 20 meters from baseline. Overall this figure shows that patients treated with Adempas benefit compared to those treated with placebo. As demonstrated in Figure 7, 193 patients receiving Adempas (76%) experienced an improvement in 6MWD compared to 74 patients (59%) on placebo.

Figure 7: PATENT-1 Distribution of Patients by Change from Baseline in 6-Minute Walk Distance

Improvements 6MWD were apparent from Week 2 onward. At Week 12, the placebo-adjusted mean increase in 6MWD within the Adempas group was 36 m (95% CI: 20 m to 52 m; p<0.0001). For PATENT-1, the median difference (Hodges-Lehmann non-parametric estimate) in 6MWD was 29 m (95% CI, 17 m to 40 m). There was an exploratory 1.5 mg capped titration arm (n = 63). The data did not suggest incremental benefit from escalating dose from 1.5 mg three times a day to 2.5 mg three times a day.

Placebo-adjusted changes in 6MWD at 12 weeks were evaluated in subgroups (see Figure 8).

Figure 8: PATENT-1 Mean Treatment Difference in Change from Baseline to Last Visit in 6-Minute Walk Distance (meter) by Prespecified Subgroups

WHO Functional Class improvements in the IDT (individual dose titration) arm of the PATENT-1 trial are shown in Table 5.

Table 5: Effects of Adempas on the Change in WHO Functional Class in PATENT-1 from Baseline to Week 12
Change in WHO Functional Class | Adempas (IDT) (n=254) | Placebo (n=125)
Improved | 53 (21%) | 18 (14%)
Stable | 192 (76%) | 89 (71%)
Deteriorated | 9 (4%) | 18 (14%)
 | p-value = 0.0033

Time to clinical worsening was a combined endpoint defined as death (all-cause mortality), heart/lung transplantation, atrial septostomy, hospitalization due to persistent worsening of pulmonary hypertension, start of new PAH-specific treatment, persistent decrease in 6MWD and persistent worsening of WHO Functional Class.

Effects of Adempas in PATENT-1 on events of clinical worsening are shown in Table 6.

Table 6: Effects of Adempas in PATENT-1 on Events of Clinical Worsening (ITT analysis set)
Clinical Worsening Events | Adempas (IDT) (n=254) | Placebo (n=126)
Patients with any clinical worsening* | 3 (1.2%) | 8 (6.3%)
- Death | 2 (0.8%) | 3 (2.4%)
- Hospitalizations due to PH | 1 (0.4%) | 4 (3.2%)
- Decrease in 6MWD due to PH | 1 (0.4%) | 2 (1.6%)
- Persistent worsening of FC due to PAH | 0 | 1 (0.8%)
- Start of new PAH treatment | 1 (0.4%) | 5 (4.0%)

* p-value=0.0285 (Mantel-Haenszel estimate)

Note: Patients may have had more than one event of clinical worsening.

Adempas-treated patients experienced a significant delay in time to clinical worsening versus placebo-treated patients (p=0.0046; Stratified log-rank test). Significantly fewer events of clinical worsening up to week 12 (last visit) were observed in patients treated with Adempas (1.2%) compared to placebo (6.3%) (p=0.0285, Mantel-Haenszel estimate).

The Kaplan-Meier plot of time to clinical worsening is presented in Figure 9.

Figure 9: PATENT-1 Time (in Days) to Clinical Worsening (ITT analysis set)

Long Term Treatment of PAH

An open label extension study (PATENT-2) included 396 patients who had completed PATENT-1. At the cut-off date in the PATENT-2 study, the mean treatment duration for the total population was 1146 days (± 479). The probabilities of survival at 1 and 2 years were 97% and 93%, respectively. Without a control group, these data must be interpreted cautiously.

16 HOW SUPPLIED/STORAGE AND HANDLING

16.1 How Supplied

Adempas (riociguat) tablets are film-coated, round, and debossed with the "Bayer cross" on one side.

 | Color | Debossing; Side 2 | NDC 50419-xxx-xx
 | Color | Debossing; Side 2 | Bottle of 9 | Bottle of 90 | Blister of 42
0.5 mg | White | 0.5 R | 250-91 | 250-01 | 250-03
1 mg | Pale yellow | 1 R | 251-91 | 251-01 | 251-03
1.5 mg | Yellow-orange | 1.5 R | 252-91 | 252-01 | 252-03
2 mg | Pale orange | 2 R | 253-91 | 253-01 | 253-03
2.5 mg | Red-orange | 2.5 R | 254-91 | 254-01 | 254-03

16.2 Storage and Handling

Store at 25°C (77°F); excursions are permitted from 15°C to 30°C (59°F to 86°F) [see USP Controlled Room Temperature].

17 PATIENT COUNSELING INFORMATION

Advise the patient to read the FDA-approved patient labeling (Medication Guide).

Embryo-Fetal Toxicity

Instruct patients on the risk of fetal harm when Adempas is used during pregnancy [see Warnings and Precautions (5.1) and Use in Specific Populations (8.1)]. Instruct females of reproductive potential to use effective contraception prior to initiation of treatment, during and for one month after stopping treatment and to contact their healthcare provider immediately if they suspect they may be pregnant. Confirm negative pregnancy status prior to starting treatment.

- Educate and counsel females of reproductive potential on the use of emergency contraception in the event of unprotected sex or contraceptive failure.
- Advise pre-pubertal females to report any changes in their reproductive status immediately to their prescriber.

Lactation

Advise women not to breastfeed during treatment with ADEMPAS [see Use in Specific Populations (8.2)].

Other Risks Associated with Adempas

- Inform patients of the contraindication of Adempas with nitrates or nitric oxide donors or PDE-5 inhibitors.
- Advise patients about the potential risks/signs of hemoptysis and to report any potential signs of hemoptysis to their physicians.
- Instruct patients on the dosing, titration, and maintenance of Adempas.
- Advise patients regarding activities that may impact the pharmacology of Adempas (strong multi pathway CYP inhibitors and P-gp/BCRP inhibitors and smoking). Instruct patients to report all current medications and new medications to their physician.
- Advise patients that antacids should not be taken within 1 hour of taking Adempas.
- Inform patients that Adempas can cause dizziness, which can affect the ability to drive and use machines [see Adverse Reactions (6.1)]. Advise patients to be aware of how they react to Adempas before driving or operating machinery, and if needed, consult their physician. Patients should consult their physicians if dizziness gets worse with Adempas.

MEDICATION GUIDE

Adempas (a-dem-pahs)
(riociguat)

tablets

Read this Medication Guide before you start taking Adempas and each time you get a refill. There may be new information. This Medication Guide does not take the place of talking to your doctor about your medical condition or your treatment.

What is the most important information I should know about Adempas?

- Serious birth defects.
  Adempas may cause serious birth defects if taken during pregnancy.
  - Females who are able to get pregnant must have a negative pregnancy status before beginning treatment with Adempas. Talk to your doctor on how to confirm negative pregnancy status. Talk to your doctor about your menstrual cycle. Your doctor will decide when to do the tests, and order the tests for you depending on your menstrual cycle.
    - Females who are able to get pregnant are females who:
      - Have entered puberty, even if they have not started their period, and
      - Have a uterus, and
      - Have not gone through menopause (have not had a period for at least 12 months for natural reasons, or who have had their ovaries removed)
    - Females who are not able to get pregnant are females who:
      - Have not yet entered puberty, or
      - Do not have a uterus, or
      - Have gone through menopause (have not had a period for at least 12 months for natural reasons, or who have had their ovaries removed)

Females who are able to get pregnant must use effective birth control before starting treatment with Adempas, during treatment with Adempas and for 1 month after stopping Adempas because the medicine may still be in the body.

- Talk with your doctor or gynecologist (a doctor who specializes in female reproduction) to find out about options for effective birth control that you may use to prevent pregnancy during treatment with Adempas.
- If you decide that you want to change the form of birth control that you use, talk with your doctor or gynecologist to be sure that you choose another effective form of birth control.

Do not have unprotected sex. Talk to your doctor or pharmacist right away if you have unprotected sex or if you think your birth control has failed. Your doctor may talk with you about using emergency birth control.

Tell your doctor right away if you miss a menstrual period or think you may be pregnant for any reason.

If you are the parent or caregiver of a female child who started taking Adempas before reaching puberty, you should check your child regularly to see if she is developing signs of puberty. Tell your doctor right away if you notice that she is developing breast buds or any pubic hair. Your doctor should decide if your child has reached puberty. Your child may reach puberty before having her first menstrual period.

If you are a female who can become pregnant, talk to your doctor to understand the benefits and risks of Adempas.

What is Adempas?

Adempas is a prescription medicine used to treat adults with:

- chronic thromboembolic pulmonary hypertension (CTEPH)
  - treated with surgery but who continue to have high pulmonary blood pressure (persistent) or it comes back after surgery (recurrent), or
  - that cannot be treated with surgery.
CTEPH is a type of high blood pressure in the arteries of your lungs caused by blood clots that narrow or block blood flow. Adempas can improve your ability to exercise and can help to improve some of your symptoms.
- pulmonary arterial hypertension (PAH)
PAH is a type of high blood pressure in the arteries of your lungs. Adempas can improve your ability to exercise, improve some of your symptoms, and help slow down the worsening of your physical condition.

It is unknown if Adempas is safe and effective in children.

Who should not take Adempas?

Do not take Adempas if:

- you are pregnant, plan to become pregnant, or become pregnant during treatment with Adempas. Adempas may cause serious birth defects. (See the Medication Guide section above called "What is the most important information I should know about Adempas?")
- you take:
  - another medicine called a soluble guanylate cyclase stimulator (sGC). Ask your healthcare provider if you are not sure if you are taking an sGC medicine.
  - a nitrate medicine to treat high blood pressure or heart disease, such as nitroglycerin, or a medicine called a nitric oxide donor, such as amyl nitrite
  - certain other medicines that contain sildenafil (Revatio or Viagra), tadalafil (Adcirca or Cialis), vardenafil (Levitra or Staxyn), dipyridamole, or theophylline. Revatio and Adcirca are also used to treat PAH
- you have pulmonary hypertension associated with idiopathic interstitial pneumonias (PH-IIP).

Ask your doctor or pharmacist if you are not sure if you take any of the medicines listed above.

What should I tell my doctor before taking Adempas?

Before you take Adempas, tell your doctor if you:

- smoke
- have recently had serious bleeding from your lung, or if you have had a medical procedure called bronchial arterial embolization to stop you from coughing up blood
- have problems with your heart or blood circulation
- have low blood pressure
- have liver problems
- have kidney problems or are on dialysis
- have narrowing of the pulmonary veins, a condition called pulmonary veno-occlusive disease or PVOD
- have any other medical conditions

Tell your doctor about all the medicines you take, including prescription and non-prescription medicines, vitamins, and herbal supplements. Adempas and other medicines may affect each other causing side effects. Do not start any new medicine until you check with your doctor.

How should I take Adempas?

Adempas will be provided to you by a certified pharmacy. Your doctor will give you complete details.

- Do not take Adempas within 24 hours of sildenafil. Do not take Adempas 24 hours before or within 48 hours after tadalafil.
- Take Adempas exactly as your doctor tells you. Do not stop taking Adempas or change your dose without talking to your doctor.
- When you begin treatment with Adempas, your blood pressure should be monitored about every 2 weeks to help your doctor decide the correct dose of medicine for you.
- Your doctor may change your dose during treatment, especially when you first start taking Adempas. It is important to tell your doctor if you have any symptoms of low blood pressure during this time, such as dizziness, lightheadedness, or fainting.
- Take Adempas 3 times each day, about 6 to 8 hours apart.
- Take Adempas with or without food.
- Do not take more than a total of 7.5 mg of Adempas in 1 day unless your doctor tells you to.
- If you take a heartburn medicine (antacid) that contains aluminum hydroxide or magnesium hydroxide, do not take it within 1 hour of taking Adempas.
- If you take too much Adempas, call your doctor right away or go to the nearest hospital emergency room.
- If you miss a dose, take your next dose of Adempas at the regular time.
- If you miss 3 or more days of treatment with Adempas, call your doctor for instructions before you restart Adempas.

What should I avoid while taking Adempas?

- Do not get pregnant while taking Adempas. (See serious birth defects section of the Medication Guide above called "What is the most important information I should know about Adempas?") If you miss a menstrual period, or think you might be pregnant, call your doctor right away.
- It is not known if Adempas passes into your breast milk. You should not breastfeed if you take Adempas. Talk to your doctor about the best way to feed your baby if you take Adempas.
- Adempas may make you feel dizzy. Do not drive, operate machinery, or do other activities that require mental alertness or coordination until you know how Adempas affects you. Talk with your doctor if you are concerned about when it is safe for you to do these activities.
- Smoking. Adempas may not work as well if you smoke during treatment. Tell your doctor if you stop smoking or start smoking during treatment with Adempas, because your dose of Adempas may need to be changed.

What are the possible side effects of Adempas?

Adempas may cause serious side effects including:

- Serious birth defects. (See "What is the most important information I should know about Adempas?")
- Reduced blood pressure. Adempas reduces blood pressure. This may cause symptoms of low blood pressure, such as lightheadedness, chest pain, and dizziness especially in people who are dehydrated, or have a severe blockage of blood flow out of the heart, or have certain other medical problems. Your doctor will check you for these problems.
- Increased risk of bleeding, including bleeding from the respiratory tract. Tell your doctor right away if you cough up blood during treatment with Adempas.
- Worsening of symptoms in people with Pulmonary Veno-Occlusive Disease (PVOD). If you have PVOD, treatment with Adempas may cause a build-up of fluid in your lungs (pulmonary edema). This may cause you to feel short of breath. Your doctor may tell you to stop taking Adempas and switch you to a different medicine.
- The most common side effects of Adempas are:
- headache
- dizziness
- indigestion
- swelling of your hands, legs, feet, and ankles (peripheral edema)
- nausea, diarrhea, and vomiting

Tell your doctor if you have any side effect that bothers you or that does not go away. These are not all the possible side effects of Adempas.

Call your doctor for medical advice about side effects. You may report side effects to FDA at 1-800-FDA-1088.

How should I store Adempas?

- Store Adempas at room temperature between 59° F to 86° F (15° C to 30° C)

Keep Adempas and all medicines out of the reach of children.

General Information about Adempas

Medicines are sometimes prescribed for purposes other than those listed in a Medication Guide. Do not use Adempas for a condition for which it is not prescribed. Do not give Adempas to other people, even if they have the same symptoms that you have. It may harm them.

This Medication Guide summarizes the most important information about Adempas. If you would like more information about Adempas, talk with your doctor. You can ask your doctor or pharmacist for information about Adempas that is written for health professionals. For more information go to www.Adempas-us.com or call 1-888-842-2937.

What are the ingredients in Adempas?

Active ingredient: riociguat

Inactive ingredients: cellulose microcrystalline, crospovidone, hypromellose 5cP, lactose monohydrate, magnesium stearate, sodium laurylsulfate, hydroxypropylcellulose, hypromellose 3cP, propylene glycol, titanium dioxide. Adempas 1 mg, 1.5 mg, 2 mg and 2.5 mg tablets also contain ferric oxide yellow. Adempas 2 mg and 2.5 mg tablets also contain ferric oxide red.

This Medication Guide has been approved by the U.S. Food and Drug Administration.

Revised x/202x

Manufactured for:

Bayer HealthCare Pharmaceuticals Inc.
Whippany, NJ 07981

Manufactured in Germany

©2013 Bayer HealthCare Pharmaceuticals Inc.

PACKAGE/LABEL PRINCIPAL DISPLAY PANEL

NDC 50419-250-01
Rx only
Adempas 0.5 mg
(riociguat) tablets
each tablet contains 0.5 mg of riociguat

Note to Dispencer: Provide a copy of the Adempas Medication Guide included in this carton to each patient and at each refill.

- 90 tablets
- for oral administration

PACKAGE/LABEL PRINCIPAL DISPLAY PANEL

NDC 50419-251-01
Rx only
Adempas 1 mg
(riociguat) tablets
each tablet contains 1 mg of riociguat

Note to Dispencer: Provide a copy of the Adempas Medication Guide included in this cartonto each patient and at each refill.

- 90 tablets
- for oral administration

PACKAGE/LABEL PRINCIPAL DISPLAY PANEL

NDC 50419-252-01
Rx only
Adempas 1.5 mg
(riociguat) tablets
each tablet contains 1.5 mg of riociguat

Note to Dispencer: Provide a copy of the Adempas Medication Guide included in this cartonto each patient and at each refill.

- 90 tablets
- for oral administration

PACKAGE/LABEL PRINCIPAL DISPLAY PANEL

NDC 50419-253-01
Rx only
Adempas 2 mg
(riociguat) tablets
each tablet contains 2 mg of riociguat

Note to Dispencer: Provide a copy of the Adempas Medication Guide included in this cartonto each patient and at each refill.

- 90 tablets
- for oral administration

PACKAGE/LABEL PRINCIPAL DISPLAY PANEL

NDC 50419-254-01
Rx only
Adempas 2.5 mg
(riociguat) tablets
each tablet contains 2.5 mg of riociguat

Note to Dispencer: Provide a copy of the Adempas Medication Guide included in this cartonto each patient and at each refill.

- 90 tablets
- for oral administration